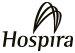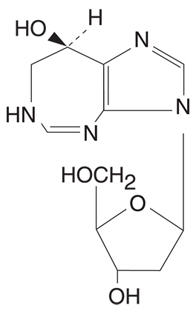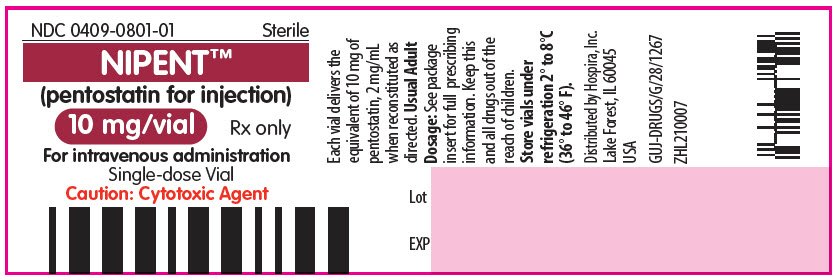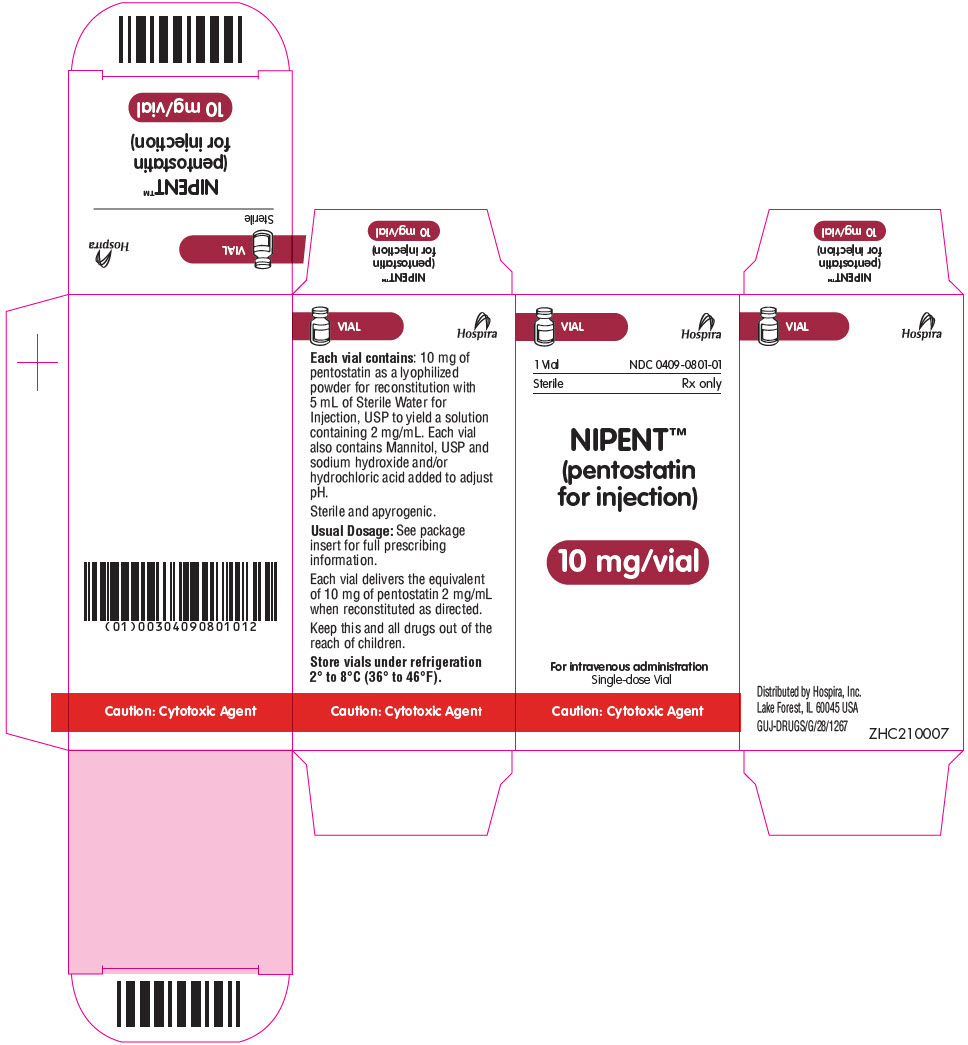 DRUG LABEL: Nipent
NDC: 0409-0801 | Form: INJECTION, POWDER, LYOPHILIZED, FOR SOLUTION
Manufacturer: Hospira, Inc.
Category: prescription | Type: HUMAN PRESCRIPTION DRUG LABEL
Date: 20251113

ACTIVE INGREDIENTS: PENTOSTATIN 2 mg/1 mL
INACTIVE INGREDIENTS: MANNITOL; SODIUM HYDROXIDE; HYDROCHLORIC ACID

NIPENT™ (pentostatin for injection)

Rx only

WARNING

NIPENT should be administered under the supervision of a physician qualified and experienced in the use of cancer chemotherapeutic agents. The use of higher doses than those specified (see DOSAGE AND ADMINISTRATION) is not recommended. Dose-limiting severe renal, liver, pulmonary, and CNS toxicities occurred in Phase 1 studies that used NIPENT at higher doses (20-50 mg/m^2 in divided doses over 5 days) than recommended.

In a clinical investigation in patients with refractory chronic lymphocytic leukemia using NIPENT at the recommended dose in combination with fludarabine phosphate, 4 of 6 patients entered in the study had severe or fatal pulmonary toxicity. The use of NIPENT in combination with fludarabine phosphate is not recommended.

DESCRIPTION

NIPENT™ (pentostatin for injection) is supplied as a sterile, apyrogenic, lyophilized powder in single-dose vials for intravenous administration. Each vial contains 10 mg of pentostatin and 50 mg of Mannitol, USP. The pH of the final product is maintained between 7.0 and 8.5 by addition of sodium hydroxide or hydrochloric acid.

Pentostatin, also known as 2'-deoxycoformycin (DCF), is a potent inhibitor of the enzyme adenosine deaminase and is isolated from fermentation cultures of Streptomyces antibioticus. Pentostatin is known chemically as (R)-3-(2-deoxy-ß-D-erythropentofuranosyl)3,6,7,8 tetrahydroimidazo[4,5d][1,3]diazepin-8-ol with a molecular formula of C11H16N4O4 and a molecular weight of 268.27. The molecular structure of pentostatin is:

Pentostatin is a white to off-white solid, freely soluble in distilled water.

CLINICAL PHARMACOLOGY

Mechanism of Action

Pentostatin is a potent transition state inhibitor of the enzyme adenosine deaminase (ADA). The greatest activity of ADA is found in cells of the lymphoid system with T-cells having higher activity than B-cells, and T-cell malignancies having higher ADA activity than B-cell malignancies. Pentostatin inhibition of ADA, particularly in the presence of adenosine or deoxyadenosine, leads to cytotoxicity, and this is believed to be due to elevated intracellular levels of dATP which can block DNA synthesis through inhibition of ribonucleotide reductase. Pentostatin can also inhibit RNA synthesis as well as cause increased DNA damage. In addition to elevated dATP, these mechanisms may also contribute to the overall cytotoxic effect of pentostatin. The precise mechanism of pentostatin's antitumor effect, however, in hairy cell leukemia is not known.

Pharmacokinetics/Drug Metabolism

A tissue distribution and whole-body autoradiography study in the rat revealed that radioactivity concentrations were highest in the kidneys with very little central nervous system penetration.

In man, following a single-dose of 4 mg/m^2 of pentostatin infused over 5 minutes, the distribution half-life was 11 minutes, the mean terminal half-life was 5.7 hours, the mean plasma clearance was 68 mL/min/m^2, and approximately 90% of the dose was excreted in the urine as unchanged pentostatin and/or metabolites as measured by adenosine deaminase inhibitory activity. The plasma protein binding of pentostatin is low, approximately 4%.

A positive correlation was observed between pentostatin clearance and creatinine clearance (CLcr) in patients with CLcr values ranging from 60 mL/min to 130 mL/min.^1 Pentostatin half-life in patients with renal impairment (CLcr <50 mL/min, n=2) was 18 hours, which was much longer than that observed in patients with normal renal function (CLcr >60 mL/min, n=14), about 6 hours.

CLINICAL STUDIES

The following table provides efficacy results for 4 groups (columns) of patients with hairy cell leukemia: patients who initially received NIPENT, patients who initially received alpha-interferon (IFN), and 2 different groups of patients who received NIPENT after proving to be refractory to, or intolerant of IFN therapy. The first 2 groups represent treatment results from the SWOG 8691 study, a large multicenter study comparing NIPENT and IFN in untreated (frontline) patients with confirmed hairy cell leukemia. The third group represents evaluable patients from the SWOG study who crossed over to NIPENT after initially receiving IFN. The fourth group, labeled NCI Phase 2 studies, displays pooled results of 2 noncomparative studies (MD Anderson and CALGB), in which NIPENT was used to treat patients with confirmed IFN-refractory disease.

In the SWOG 8691 study, NIPENT was administered at a dose of 4 mg/m^2 every 2 weeks. After 6 months of treatment, patients were evaluated for response. If a complete response was achieved, 2 additional doses of NIPENT were administered and then discontinued. If a partial response was achieved, NIPENT was continued for up to an additional 6 months. NIPENT was discontinued for stable disease after 6 months or progressive disease after 2 months of therapy. IFN was administered 3 million units subcutaneously 3 times per week. Patients who achieved a complete or partial response after 6 months of treatment continued on IFN for another 6 months. IFN was discontinued if patients did not achieve a complete or partial response after 6 months of initial treatment or progressed after 2 months. This study allowed crossover of patients intolerant of, or refractory to, initial treatment.

Interferon-refractory patients enrolled into the MD Anderson study received NIPENT at a dose of 4 mg/m^2 every other week for 3 months and responding patients received 3 additional months. CALGB patients received 4 mg/m^2 of NIPENT every other week for 3 months and responding patients were treated monthly for up to 9 additional months. Almost all patients had a PS of 0 to 2 in the Phase 2 and 3 studies.

For each study, a complete response (CR) required clearing of the peripheral blood and bone marrow of all hairy cells, normalization of organomegaly and lymphadenopathy by physical examination, and recovery of hemoglobin to at least 12 g/dL, platelet count to at least 100,000/mm^3, and granulocyte count to at least 1500/mm^3. A partial response (PR) required that the percentage of hairy cells in the blood and bone marrow decrease by more than 50%, enlarged organs and lymph nodes decrease by more than 50% by physical examination, and hematologic parameters had to meet the same criteria as for complete response. The table below reports the response rate for 2 groups of patients: (1) Evaluable, i.e., patients who could be evaluated for response and (2) Intent-to-Treat, i.e., patients diagnosed with hairy cell leukemia.

 | FRONTLINE |  | IFN-REFRACTORY [Evaluable patients]
Parameter | Evaluable; NIPENT; N = 138 | Evaluable; IFN; N=130 | SWOG 8691 [Patients either refractory to, or intolerant of, IFN]; Crossover; N=79 | NCI Phase 2; Studies; N=44
Response Rates (%)
Evaluable CR | 84 | 18 | 85 | 58
PR | 6 | 24 | 4 | 28
Intent-to-Treat | N=170 | N=170
CR | 68 | 14
PR | 5 | 18
Median Time to Response (months)
CR | 6.6 | 11.5 | 6.0 | 4.2
PR | 4.0 | 6.2 | 5.8 | —
Median Duration of Response (months)
CR | NR | 8.3 | NR | >7.7 [Kaplan-Meier estimate] (CALGB); >15.2 (MDA)
PR | NR | 15.2 | NR | —
% Estimated to be in Response After 24 Months
CR | 76 | 16 | 85 | —
PR | 50 | 21 | — | —
Median Time to Recovery (days)
ANC (1500/mm^3) | 70 | 106 | — | —
Platelets (100,000/mm^3) | 22 | 36 | — | —
NR = Not reached by Kaplan-Meier method; ANC = Absolute neutrophil count.

The results show that frontline patients treated with NIPENT achieved a significantly higher rate of response than those treated with IFN. The time to recovery of neutrophil and platelet counts was shorter with NIPENT treatment and the estimated duration of response was longer. The response rate in IFN-refractory patients treated with NIPENT was similar to that in NIPENT-treated frontline patients. At a median follow-up duration of 46 months, there was no statistically significant difference in survival between hairy cell leukemia patients initially treated with NIPENT and those initially treated with IFN. However, no definite conclusions regarding survival can be made from these results because they are complicated by the fact that the majority of IFN patients crossed over to NIPENT treatment.

In the Phase 3 SWOG study, 25 patients with hairy cell leukemia died during treatment or follow-up: 18 patients had last received NIPENT (3 of whom had crossed over from IFN), and 7 patients had last received IFN (1 of whom crossed over from NIPENT). Eleven of the 25 deaths occurred within 60 days of the last dose of treatment. Of these, hairy cell leukemia was cited by the investigators as a contributory cause for 1 death in the NIPENT group and 3 deaths in the IFN group. Additionally, infection contributed to the deaths of 3 patients in the NIPENT group and 2 patients in the IFN group. Approximately 4% of hairy cell leukemia patients, in each arm, died more than 60 days after the last dose of either treatment and there was no outstanding cause of death among these patients.

INDICATIONS AND USAGE

NIPENT is indicated as single-agent treatment for both untreated and alpha-interferon-refractory hairy cell leukemia patients with active disease as defined by clinically significant anemia, neutropenia, thrombocytopenia, or disease-related symptoms.

CONTRAINDICATIONS

NIPENT is contraindicated: In patients who have demonstrated hypersensitivity to NIPENT.

WARNINGS

See Boxed Warning.

Patients with hairy cell leukemia may experience myelosuppression primarily during the first few courses of treatment. Patients with infections prior to NIPENT treatment have in some cases developed worsening of their condition leading to death, whereas others have achieved complete response. Patients with infection should be treated only when the potential benefit of treatment justifies the potential risk to the patient. Efforts should be made to control the infection before treatment is initiated or resumed.

In patients with progressive hairy cell leukemia, the initial courses of NIPENT treatment were associated with worsening of neutropenia. Therefore, frequent monitoring of complete blood counts during this time is necessary. If severe neutropenia continues beyond the initial cycles, patients should be evaluated for disease status, including a bone marrow examination.

Elevations in liver function tests occurred during treatment with NIPENT and were generally reversible.

Renal toxicity was observed at higher doses in early studies; however, in patients treated at the recommended dose, elevations in serum creatinine were usually minor and reversible. There were some patients who began treatment with normal renal function who had evidence of mild to moderate toxicity at a final assessment (See DOSAGE AND ADMINISTRATION).

Rashes, occasionally severe, were commonly reported and may worsen with continued treatment. Withholding of treatment may be required (See DOSAGE AND ADMINISTRATION).

Acute pulmonary edema and hypotension, leading to death, have been reported in the literature in patients treated with pentostatin in combination with carmustine, etoposide and high dose cyclophosphamide as part of the ablative regimen for bone marrow transplant.

Pregnancy

Pentostatin can cause fetal harm when administered to a pregnant woman. Pentostatin was administered intravenously at doses of 0, 0.01, 0.1, or 0.75 mg/kg/day (0, 0.06, 0.6, and 4.5 mg/m^2) to pregnant rats on days 6 through 15 of gestation. Drug-related maternal toxicity occurred at doses of 0.1 and 0.75 mg/kg/day (0.6 and 4.5 mg/m^2). Teratogenic effects were observed at 0.75 mg/kg/day (4.5 mg/m^2) manifested by increased incidence of various skeletal malformations. In a dose range-finding study, pentostatin was administered intravenously to rats at doses of 0, 0.05, 0.1, 0.5, 0.75, or 1 mg/kg/day (0, 0.3, 0.6, 3, 4.5, 6 mg/m^2), on days 6 through 15 of gestation. Fetal malformations that were observed were an omphalocele at 0.05 mg/kg (0.3 mg/m^2), gastroschisis at 0.75 mg/kg and 1 mg/kg (4.5 and 6 mg/m^2), and a flexure defect of the hindlimbs at 0.75 mg/kg (4.5 mg/m^2). Pentostatin was also shown to be teratogenic in mice when administered as a single 2 mg/kg (6 mg/m^2) intraperitoneal injection on day 7 of gestation. Pentostatin was not teratogenic in rabbits when administered intravenously on days 6 through 18 of gestation at doses of 0, 0.005, 0.01, or 0.02 mg/kg/day (0, 0.015, 0.03, or 0.06 mg/m^2); however maternal toxicity, abortions, early deliveries, and deaths occurred in all drug-treated groups. There are no adequate and well-controlled studies in pregnant women. If NIPENT is used during pregnancy, or if the patient becomes pregnant while taking (receiving) this drug, the patient should be apprised of the potential hazard to the fetus. Women of childbearing potential receiving NIPENT should be advised to avoid becoming pregnant.

PRECAUTIONS

General

Therapy with NIPENT requires regular patient observation and monitoring of hematologic parameters and blood chemistry values. If severe adverse reactions occur, the drug should be withheld (see DOSAGE AND ADMINISTRATION), and appropriate corrective measures should be taken according to the clinical judgment of the physician.

NIPENT treatment should be withheld or discontinued in patients showing evidence of nervous system toxicity.

Information for Patients

Patients should be advised of the signs and symptoms of adverse events associated with NIPENT therapy (See ADVERSE REACTIONS).

Laboratory Tests

Prior to initiating therapy with NIPENT, renal function should be assessed with a serum creatinine and/or a CLcr assay (See CLINICAL PHARMACOLOGY and DOSAGE AND ADMINISTRATION). Complete blood counts and serum creatinine should be performed before each dose of NIPENT and at other appropriate periods during therapy (see DOSAGE AND ADMINISTRATION). Severe neutropenia has been observed following the early courses of treatment with NIPENT and therefore frequent monitoring of complete blood counts is recommended during this time. If hematologic parameters do not improve with subsequent courses, patients should be evaluated for disease status, including a bone marrow examination. Periodic monitoring of the peripheral blood for hairy cells should be performed to assess the response to treatment.

In addition, bone marrow aspirates and biopsies may be required at 2 to 3 month intervals to assess the response to treatment.

Drug Interactions

Allopurinol and NIPENT are both associated with skin rashes. Based on clinical studies in 25 refractory patients who received both NIPENT and allopurinol, the combined use of NIPENT and allopurinol did not appear to produce a higher incidence of skin rashes than observed with NIPENT alone. There has been a report of one patient who received both drugs and experienced a hypersensitivity vasculitis that resulted in death. It was unclear whether this adverse event and subsequent death resulted from the drug combination.

Biochemical studies have demonstrated that pentostatin enhances the effects of vidarabine, a purine nucleoside with antiviral activity. The combined use of vidarabine and NIPENT may result in an increase in adverse reactions associated with each drug. The therapeutic benefit of the drug combination has not been established.

The combined use of NIPENT and fludarabine phosphate is not recommended because it may be associated with an increased risk of fatal pulmonary toxicity (see WARNINGS).

Acute pulmonary edema and hypotension, leading to death, have been reported in the literature in patients treated with pentostatin in combination with carmustine, etoposide and high dose cyclophosphamide as part of the ablative regimen for bone marrow transplant.

Carcinogenesis, Mutagenesis, Impairment of Fertility

Carcinogenesis: No animal carcinogenicity studies have been conducted with pentostatin.

Mutagenesis: Pentostatin was nonmutagenic when tested in Salmonella typhimurium strains TA-98, TA-1535, TA-1537, and TA-1538. When tested with strain TA-100, a repeatable statistically significant response trend was observed with and without metabolic activation. The response was 2.1 to 2.2 fold higher than the background at 10 mg/plate, the maximum possible drug concentration. Formulated pentostatin was clastogenic in the in vivo mouse bone marrow micronucleus assay at 20, 120, and 240 mg/kg. Pentostatin was not mutagenic to V79 Chinese hamster lung cells at the HGPRT locus exposed 3 hours to concentrations of 1 to 3 mg/mL, with or without metabolic activation. Pentostatin did not significantly increase chromosomal aberrations in V79 Chinese hamster lung cells exposed 3 hours to 1 to 3 mg/mL in the presence or absence of metabolic activation.

Impairment of Fertility: No fertility studies have been conducted in animals; however, in a 5-day intravenous toxicity study in dogs, mild seminiferous tubular degeneration was observed with doses of 1 and 4 mg/kg. The possible adverse effects on fertility in humans have not been determined. Advise patients on the potential risks for infertility.

Contraception in Males and Females

Due to the genotoxicity and embryo-fetal toxicity findings in nonclinical studies, advise females of reproductive potential to use effective contraception during treatment and for 6 months following the last dose of NIPENT.

Due to the genotoxicity findings in nonclinical studies, advise male patients with female partners of reproductive potential to use effective contraception during treatment and for 3 months following the last dose of NIPENT.

Pregnancy

(See WARNINGS)

Nursing Mothers

It is not known whether NIPENT is excreted in human milk. Because many drugs are excreted in human milk, and because of the potential for serious adverse reactions in the breast-fed child due to pentostatin, advise patients not to breast-feed while on NIPENT therapy and for 1 week following the last dose of treatment.

Pediatric Use

Safety and effectiveness in children or adolescents have not been established.

ADVERSE REACTIONS

Most patients treated for hairy cell leukemia in the five NCI-sponsored Phase 2 studies and the Phase 3 SWOG study experienced an adverse event. The following table lists the most frequently occurring adverse events in patients treated with NIPENT (both frontline and IFN-refractory patients) compared with IFN (frontline only), regardless of drug association. The drug association of some adverse events is uncertain as they may be associated with the disease itself (e.g., infection, hematologic suppression), but other events, such as the gastrointestinal symptoms, rashes, and abnormal liver function tests, can in many cases be attributed to the drug. Most adverse events that were assessed for severity were either mild or moderate, and diminished in frequency with continued therapy.

 | Percent of Patients
All Adverse Events [Occurring in more than 10% of patients, in any group, regardless of drug association] | Frontline,; Treated; With NIPENT; N=180 | Frontline,; Treated; With IFN; N=176 | IFN-Refractory,; Treated With; NIPENT; N=197
Nausea and/or Vomiting | 63 | 22 | 53 [Includes only nausea with vomiting]
Fever | 46 | 59 | 42
Rash | 43 | 30 | 26
Fatigue | 42 | 55 | 29
Leukopenia | 22 | 15 | 60
Pruritus | 21 | 6 | 10
Coughing/Increased Cough | 20 | 15 | 17
Myalgia | 19 | 36 | 11
Chills | 19 | 34 | 11
Headache | 17 | 29 | 13
Diarrhea | 17 | 17 | 15
Abdominal Pain | 16 | 15 | 4
Anorexia | 13 | 10 | 16
Upper Respiratory Infection | 13 | 8 | 16
Asthenia | 12 | 13 | 10
Stomatitis | 12 | 7 | 5
Rhinitis | 11 | 15 | 10
Dyspnea | 11 | 13 | 8
Anemia | 8 | 5 | 35
Pain | 8 | 19 | 20
Pharyngitis | 8 | 11 | 10
Sweating/Increased Sweating | 8 | 21 | 10
Viral Infection | 8 | 17 | NR
Infection | 7 [These figures represent only unspecified infections. Refer to infection table.] | 2 | 36
Arthralgia | 6 | 14 | 3
Thrombocytopenia | 6 | 6 | 32
Skin Disorder | 4 | 5 | 17
Allergic Reaction | 2 | 1 | 11
Hepatic Disorder/Elevated Liver Function Tests [Elevated liver enzymes and liver disorder for SWOG] | 2 | 2 | 19
Neurologic Disorder, CNS/CNS Toxicity | 1 | NR | 11
Lung Disorder/Disease | NR | 1 | 12
Nausea | NR | NR | 22
Genitourinary Disorder | NR | NR | 15
NR = Not Reported

The total incidence for all types of infections is considerably higher for both treatment groups in the SWOG 8691 study than is listed in the table above. An intent-to-treat analysis of infections found that 38% of patients treated with NIPENT and 34% of patients treated with IFN averaged 2.4 and 1.9 documented infections during treatment, respectively. The following table lists the different types of infections that were reported as adverse events during the initial phase of the SWOG study. There were no apparent differences in the types of infection between the 2 treatment groups, with the possible exception of herpes zoster which was reported more frequently for NIPENT (8%) than for IFN (1%).

 | Percent of Patients
Type of Infection | Frontline, Treated; With NIPENT; N=180 | Frontline, Treated; With IFN; N=176
Upper Respiratory Infection | 13 | 8
Rhinitis | 11 | 15
Herpes Zoster | 8 | 1
Pharyngitis | 8 | 11
Viral Infection | 8 | 17
Infection (Unspecified) | 7 | 2
Sinusitis | 6 | 4
Cellulitis | 6 | 3
Bacterial Infection | 5 | 4
Pneumonia | 5 | 7
Conjunctivitis | 4 | 2
Furunculosis | 4 | <1
Herpes Simplex | 4 | 1
Bronchitis | 3 | 2
Sepsis | 3 | 2
Urinary Tract Infection | 3 | 3
Abscess, Skin | 2 | 4
Moniliasis, Oral | 2 | <1
Mycotic Infection, Skin | <1 | 3
Osteomyelitis | 1 | 0

The drug relatedness of the adverse events listed below cannot be excluded. The following adverse events occurred in 3% to 10% of NIPENT-treated patients in the initial phase of the SWOG study:

Body as a Whole—Chest Pain, Death, Face Edema, Peripheral Edema

Cardiovascular System—Hemorrhage, Hypotension

Digestive System—Dental Abnormalities, Dyspepsia, Flatulence, Gingivitis

Hematologic System—Agranulocytosis

Laboratory Deviations—Elevated Creatinine

Musculoskeletal System—Arthralgia

Nervous System—Confusion, Dizziness, Insomnia, Paresthesia, Somnolence

Psychobiologic Function—Anxiety, Depression, Nervousness

Respiratory System—Asthma

Skin & Appendages—Skin Dry, Urticaria

The remaining adverse events which occurred in less than 3% of NIPENT-treated patients during the initial phase of the SWOG study:

Body as a Whole—Flu-like Symptoms, Hangover Effect, Neoplasm

Cardiovascular System—Angina Pectoris, Arrhythmia, A-V Block, Bradycardia, Extrasystoles Ventricular, Heart Arrest, Heart Failure, Hypertension, Pericardial Effusion, Phlebitis, Pulmonary Embolus, Sinus Arrest, Tachycardia, Thrombophlebitis Deep, Vasculitis

Digestive System—Constipation, Dysphagia, Glossitis, Ileus

Hematologic System—Acute Leukemia, Anemia-Hemolytic, Aplastic Anemia

Laboratory Deviations—Hypercalcemia, Hyponatremia

Musculoskeletal System—Arthritis, Gout

Nervous System—Amnesia, Ataxia, Convulsions, Dreaming Abnormal, Dysarthria, Encephalitis, Hyperkinesia, Meningism, Neuralgia, Neuritis, Neuropathy, Paralysis, Syncope, Twitching, Vertigo

Psychobiologic Function—Decrease/Loss Libido, Emotional Lability, Hallucination, Hostility, Neurosis, Thinking Abnormal

Respiratory System—Bronchospasm, Larynx Edema

Skin and Appendages—Acne, Alopecia, Eczema, Petechial Rash, Photosensitivity Reaction

Special Senses—Amblyopia, Deafness, Earache, Eyes Dry, Labyrinthitis, Lacrimation Disorder, Nonreactive Eye, Photophobia, Retinopathy, Tinnitus, Unusual Taste, Vision Abnormal, Watery Eyes

Urogenital System—Amenorrhea, Breast Lump, Impotence, Kidney Function Abnormal, Nephropathy, Renal Failure, Renal Insufficiency, Renal Stone

One patient with hairy cell leukemia treated with NIPENT during another clinical study developed unilateral uveitis with vision loss.

Nineteen (5%) patients withdrew from the Phase 3 SWOG 8691 study because of adverse events; 9 during initial NIPENT treatment, 4 during NIPENT crossover, 5 during initial IFN treatment, and 1 during both initial IFN treatment and NIPENT crossover. In the Phase 2 studies in IFN-refractory hairy cell leukemia, 11% of patients withdrew from treatment with NIPENT due to an adverse event.

Postmarketing Experience

The following adverse reactions have been identified during post-approval use of NIPENT. Because these reactions are reported voluntarily from a population of uncertain size, it is not always possible to reliably estimate their frequency or establish a causal relationship to drug exposure.

Hematologic System—Febrile Neutropenia, Hemolytic Uremic Syndrome, Thrombotic Thrombocytopenic Purpura, Autoimmune Thrombocytopenia

Respiratory System—Acute Respiratory Failure

Skin and Appendages—Exfoliative Dermatitis

OVERDOSAGE

No specific antidote for NIPENT overdose is known. NIPENT administered at higher doses (20- 50 mg/m^2 in divided doses over 5 days) than recommended was associated with deaths due to severe renal, hepatic, pulmonary, and CNS toxicity. In case of overdose, management would include general supportive measures through any period of toxicity that occurs.

DOSAGE AND ADMINISTRATION

It is recommended that patients receive hydration with 500 to 1,000 mL of 5% Dextrose in 0.5 Normal Saline or equivalent before NIPENT administration. An additional 500 mL of 5% Dextrose or equivalent should be administered after NIPENT is given.

The recommended dosage of NIPENT for the treatment of hairy cell leukemia is 4 mg/m^2 every other week. NIPENT may be administered intravenously by bolus injection or diluted in a larger volume and given over 20 to 30 minutes (See Preparation of Intravenous Solution).

Higher doses are not recommended.

No extravasation injuries were reported in clinical studies.

The optimal duration of treatment has not been determined. In the absence of major toxicity and with observed continuing improvement, the patient should be treated until a complete response has been achieved. Although not established as required, the administration of two additional doses has been recommended following the achievement of a complete response.

All patients receiving NIPENT at 6 months should be assessed for response to treatment. If the patient has not achieved a complete or partial response, treatment with NIPENT should be discontinued.

If the patient has achieved a partial response, NIPENT treatment should be continued in an effort to achieve a complete response. At any time thereafter that a complete response is achieved, two additional doses of NIPENT are recommended. NIPENT treatment should then be stopped. If the best response to treatment at the end of 12 months is a partial response, it is recommended that treatment with NIPENT be stopped.

Withholding or discontinuation of individual doses may be needed when severe adverse reactions occur. Drug treatment should be withheld in patients with severe rash, and withheld or discontinued in patients showing evidence of nervous system toxicity.

NIPENT treatment should be withheld in patients with active infection occurring during the treatment but may be resumed when the infection is controlled.

Patients who have elevated serum creatinine should have their dose withheld and a CLcr determined. There are insufficient data to recommend a starting or a subsequent dose for patients with impaired renal function (CLcr <60 mL/min).

Patients with impaired renal function should be treated only when the potential benefit justifies the potential risk. Two patients with impaired renal function (CLcr 50 to 60 mL/min) achieved complete response without unusual adverse events when treated with 2 mg/m^2.

No dosage reduction is recommended at the start of therapy with NIPENT in patients with anemia, neutropenia, or thrombocytopenia. In addition, dosage reductions are not recommended during treatment in patients with anemia and thrombocytopenia if patients can be otherwise supported hematologically. NIPENT should be temporarily withheld if the absolute neutrophil count falls during treatment below 200 cells/mm^3 in a patient who had an initial neutrophil count greater than 500 cells/mm^3 and may be resumed when the count returns to predose levels.

Preparation of Intravenous Solution

1. Procedures for proper handling and disposal of anticancer drugs should be followed. Several guidelines on this subject have been published.^2-7 There is no general agreement that all of the procedures recommended in the guidelines are necessary or appropriate. Spills and wastes should be treated with a 5% sodium hypochlorite solution prior to disposal.
2. Protective clothing including polyethylene gloves must be worn.
3. Transfer 5 mL of Sterile Water for Injection USP to the vial containing NIPENT and mix thoroughly to obtain complete dissolution of a solution yielding 2 mg/mL. Parenteral drug products should be inspected visually for particulate matter and discoloration prior to administration.
4. NIPENT may be given intravenously by bolus injection or diluted in a larger volume (25 to 50 mL) with 5% Dextrose Injection USP or 0.9% Sodium Chloride Injection USP. Dilution of the entire contents of a reconstituted vial with 25 mL or 50 mL provides a pentostatin concentration of 0.33 mg/mL or 0.18 mg/mL, respectively, for the diluted solutions.
5. NIPENT solution when diluted for infusion with 5% Dextrose Injection USP or 0.9% Sodium Chloride Injection USP does not interact with PVC infusion containers or administration sets at concentrations of 0.18 mg/mL to 0.33 mg/mL.

Stability

NIPENT vials are stable at refrigerated storage temperature 2° to 8° C (36° to 46°F) for the period stated on the package. Vials reconstituted or reconstituted and further diluted as directed may be stored at room temperature and ambient light but should be used within 8 hours because NIPENT contains no preservatives.

HOW SUPPLIED

NIPENT (pentostatin for injection) is supplied as a sterile lyophilized white to off-white powder in single-dose vials containing 10 mg of pentostatin. The vials are packed in individual cartons. NDC 0409-0801-01.

Storage: Store NIPENT vials under refrigerated storage conditions 2° to 8° C (36° to 46°F).

REFERENCES

1. Malspeis L, et al. Clinical pharmacokinetics of 2'-Deoxycoformycin. Cancer Treatment Symposia 2:7-15, 1984
2. Recommendations for the safe handling of parenteral antineoplastic drugs. NIH Publication 83-2621. For sale by the Superintendent of Documents, US Government Printing Office, Washington, DC 20402.
3. AMA council Report. Guidelines for handling parenteral antineoplastics. JAMA 253:1590-2, 1985.
4. National Study Commission on Cytotoxic Exposure—Recommendations for Handling Cytotoxic Agents. Available from Louis P. Jeffrey, Sc.D., Chairman, National Study Commission on Cytotoxic Exposure, Massachusetts College of Pharmacy and Allied Health Sciences, 179 Longwood Avenue, Boston, Massachusetts 02115.
5. Clinical Oncological Society of Australia: Guidelines and recommendations for safe handling of antineoplastic agents. Med J Australia 1:426-8, 1983.
6. Jones RB, et al. Safe handling of chemotherapeutic agents: A report from the Mount Sinai Medical Center. CA: A Cancer Journal for Clinicians 33:258-63, 1983.
7. American Society of Hospital Pharmacists technical assistance bulletin on handling cytotoxic and hazardous drugs. Am J Hosp Pharm 47:1033-49, 1990.

Distributed by Hospira, Inc.
Lake Forest, IL 60045 USA

LAB-1220-4.0

Revised: 11/2025

PRINCIPAL DISPLAY PANEL - 10 mg Vial Label

NDC 0409-0801-01
Sterile

NIPENT™
(pentostatin for injection)

10 mg/vial
Rx only

For intravenous administration
Single-dose Vial
Caution: Cytotoxic Agent

PRINCIPAL DISPLAY PANEL - 10 mg Vial Carton

VIAL
Hospira

1 Vial
NDC 0409-0801-01

Sterile
Rx only

NIPENT™
(pentostatin
for injection)

10 mg/vial

For intravenous administration
Single-dose Vial

Caution: Cytotoxic Agent